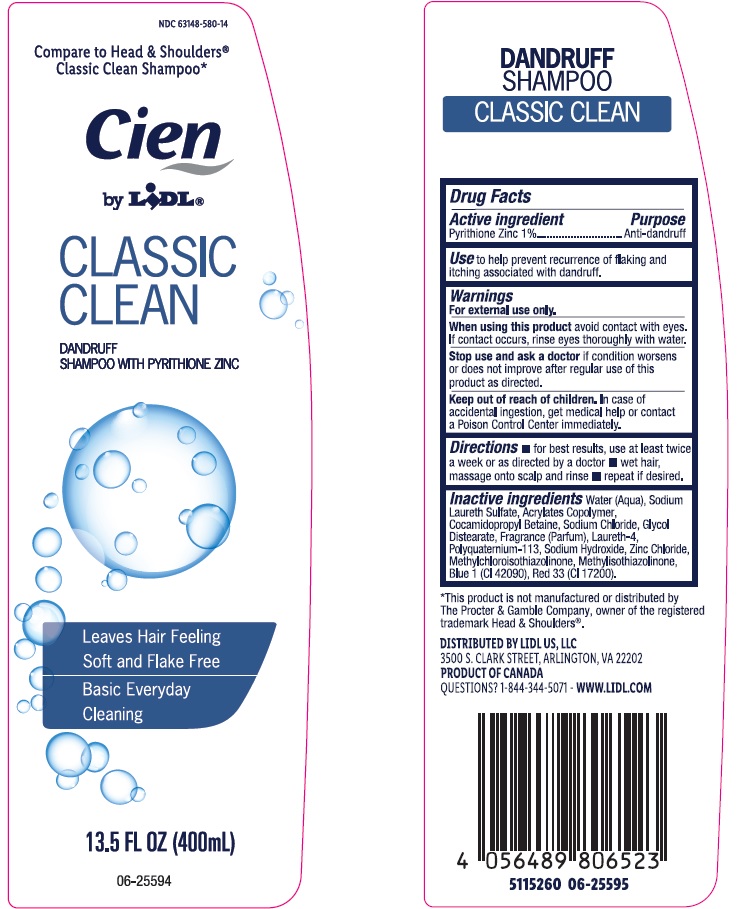 DRUG LABEL: Classic Clean
NDC: 63148-580 | Form: SHAMPOO
Manufacturer: Apollo Health and Beauty Care
Category: otc | Type: HUMAN OTC DRUG LABEL
Date: 20250207

ACTIVE INGREDIENTS: PYRITHIONE ZINC 1000 mg/100 mL
INACTIVE INGREDIENTS: COCAMIDOPROPYL BETAINE; SODIUM CHLORIDE; GLYCOL DISTEARATE; FRAGRANCE CLEAN ORC0600327; WATER; SODIUM LAURETH SULFATE; BLUE 1; LAURETH-4; SODIUM HYDROXIDE; ZINC CHLORIDE; RED 33; METHYLCHLOROISOTHIAZOLINONE; METHYLISOTHIAZOLINONE; POLYQUATERNIUM-1; ACRYLIC ACID/SODIUM ACRYLATE COPOLYMER (1:1; 600 MPA.S AT 0.2%)

NDC-63148-580, Cien Classic Clean Dandruff Shampoo

Active Ingredient

Pyrithione Zinc (1%)

Purpose

Anti-dandruff

Uses

To help prevent recurrence of flaking and itching associated with dandruff.

Warnings

For External use only.

When using this product avoid contact with eyes. If contact occurs, rinse eyes thoroughly with water.

Stop use and ask a doctor if condition worsens or does not improve after regular use of this product as directed.

Keep ot of reach of Children. In case of accidental ingestion, gety medical help or contact a Poison Control Center immediately.

Directions

- For best results, use at least twice a week or as directed by a Doctor.
- Wet hair, massage onto scalp and rinse
- repeat if desired.

Inactive Ingredients

Water (Aqua), Sodium Laureth Sulfate, Acrylates Copolymer, Cocamidopropyl Betaine, Sodium Chloride, Glycol Distearate, Fragrance (Parfum), Laureth-4, Polyquaternium-113, Sodium Hydroxide, Zinc Chloride, Methylchloroisothiazolinone, Methylisothiazolinone, Blue 1 (CI 42090), Red 33 (CI 17200).

Questions?

1-844-344-5071